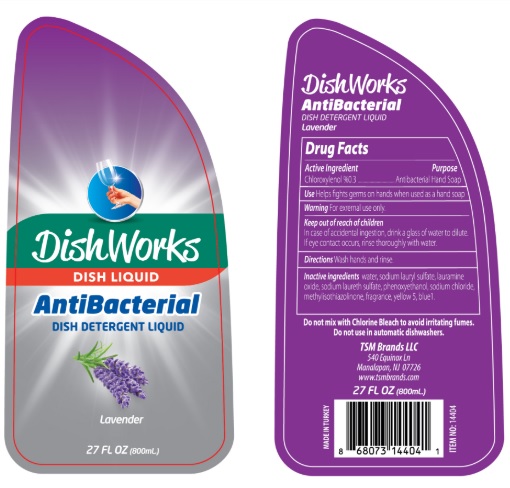 DRUG LABEL: DishWorks
NDC: 76772-002 | Form: LIQUID
Manufacturer: TSM ITHALAT IHRACAT SANAYI VE DIS TICARET LIMITED SIRKETI
Category: otc | Type: HUMAN OTC DRUG LABEL
Date: 20200430

ACTIVE INGREDIENTS: CHLOROXYLENOL 3.09 g/1 mL
INACTIVE INGREDIENTS: WATER; LAURAMINE OXIDE; SODIUM LAURETH SULFATE; SODIUM LAURYL SULFATE; SODIUM CHLORIDE; PHENOXYETHANOL; METHYLISOTHIAZOLINONE; FD&C YELLOW NO. 5; FD&C BLUE NO. 1

DishWorks Antibacterial dish detergent: Lavender

Active ingredient

Chloroxylenol 0.3% ......................... Antibacterial Hand soap

Purpose

Antibacterial Hand Soap

Use

Helps fighting germs on hands when used as hand soap

Warnings

For external use only: hands only

When using this product

- do not get into eyes. If contact occurs, rinse eyes thoroughly with water
- Do not mix with Chlorine Bleach to avoid irritating fumes. Do not use in automatic dishwashers

Stop use and ask a doctor if

- irritation or redness develops
- condition persists for more than 72 hours
- In case of accidental ingestion, drink a glass of water to dilute

Keep out of reach of children

If swallowed, get medical help or contact a Poison Control Center right away

Directions

- wet hands
- apply palmful to hands
- scrub thoroughly
- rinse thoroughly

Inactive ingredients

water, lauramine oxide, sodium laureth sulfate, sodium lauryl sulfate, sodium, sodium chloride, alcohol, fragrance, phenoxyethanol, citric acid, methylisothiazolinone, yellow 5, blue 1

WARNING

NOT FOR USE IN DISHWASHERS.

DO NOT ADD BLEACH

Made in Turkey